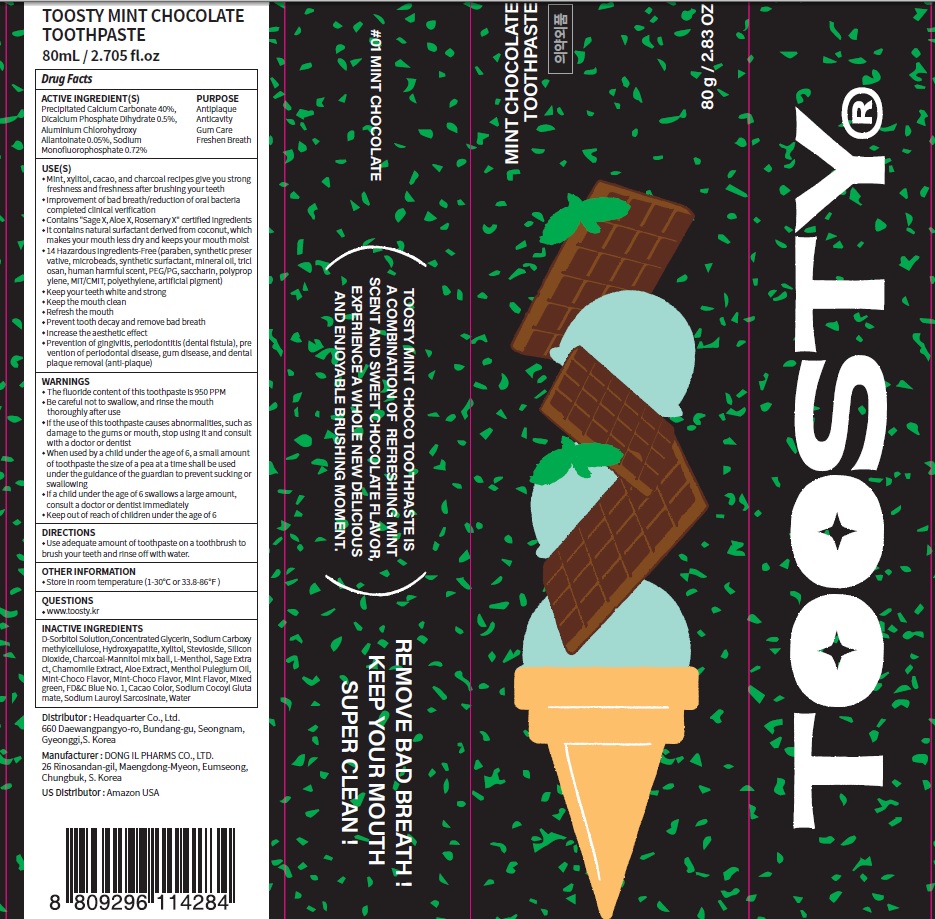 DRUG LABEL: Toosty Mint Chocolate Toothpaste
NDC: 82662-050 | Form: PASTE, DENTIFRICE
Manufacturer: Headquarter Co., Ltd
Category: otc | Type: HUMAN OTC DRUG LABEL
Date: 20230726

ACTIVE INGREDIENTS: Calcium Carbonate 40.0 g/100 g; DIBASIC CALCIUM PHOSPHATE DIHYDRATE 0.5 g/100 g; ALCLOXA 0.05 g/100 g; Sodium Monofluorophosphate 0.72 g/100 g
INACTIVE INGREDIENTS: Sorbitol; Glycerin; CARBOXYMETHYLCELLULOSE SODIUM, UNSPECIFIED

ACTIVE INGREDIENTS

Precipitated Calcium Carbonate 40%
Dicalcium Phosphate Dihydrate 0.5%
Aluminium Chlorohydroxy Allantoinate 0.05%
Sodium Monofluorophosphate 0.72%

INACTIVE INGREDIENTS

D-Sorbitol Solution,Concentrated Glycerin, Sodium Carboxymethylcellulose, Hydroxyapatite, Xylitol, Stevioside, Silicon Dioxide, Charcoal-Mannitol mix ball, L-Menthol, Sage Extract, Chamomile Extract, Aloe Extract, Menthol Pulegium Oil, Mint-Choco Flavor, Mint-Choco Flavor, Mint Flavor, Mixed green, FD&C Blue No. 1, Cacao Color, Sodium Cocoyl Glutamate, Sodium Lauroyl Sarcosinate, Water

PURPOSE

Antiplaque
Anticavity
Gum Care
Freshen Breath

WARNINGS

■ The fluoride content of this toothpaste is 950 PPM
■ Be careful not to swallow, and rinse the mouth thoroughly after use
■ If the use of this toothpaste causes abnormalities, such as damage to the gums or mouth, stop using it and consult with a doctor or dentist
■ When used by a child under the age of 6, a small amount of toothpaste the size of a pea at a time shall be used under the guidance of the guardian to prevent sucking or swallowing
■ If a child under the age of 6 swallows a large amount, consult a doctor or dentist immediately
■ Keep out of reach of children under the age of 6

Keep out of reach of children under the age of 6

Uses

■ Mint, xylitol, cacao, and charcoal recipes give you strong freshness and freshness after brushing your teeth
■ Improvement of bad breath/reduction of oral bacteria completed clinical verification
■ Contains "Sage X, Aloe X, Rosemary X" certified ingredients
■ It contains natural surfactant derived from coconut, which makes your mouth less dry and keeps your mouth moist
■ 14 Hazardous Ingredients-Free (paraben, synthetic preservative, microbeads, synthetic surfactant, mineral oil, triclosan, human harmful scent, PEG/PG, saccharin, polypropylene, MIT/CMIT, polyethylene, artificial pigment)
■ Keep your teeth white and strong
■ Keep the mouth clean
■ Refresh the mouth
■ Prevent tooth decay and remove bad breath
■ Increase the aesthetic effect
■ Prevention of gingivitis, periodontitis (dental fistula), prevention of periodontal disease, gum disease, and dental plaque removal (anti-plaque)

Directions

■ Use adequate amount of toothpaste on a toothbrush to brush your teeth and rinse off with water.

Other Information

■ Store in room temperature (1-30℃ or 33.8-86℉)

Questions

■ www.toosty.kr